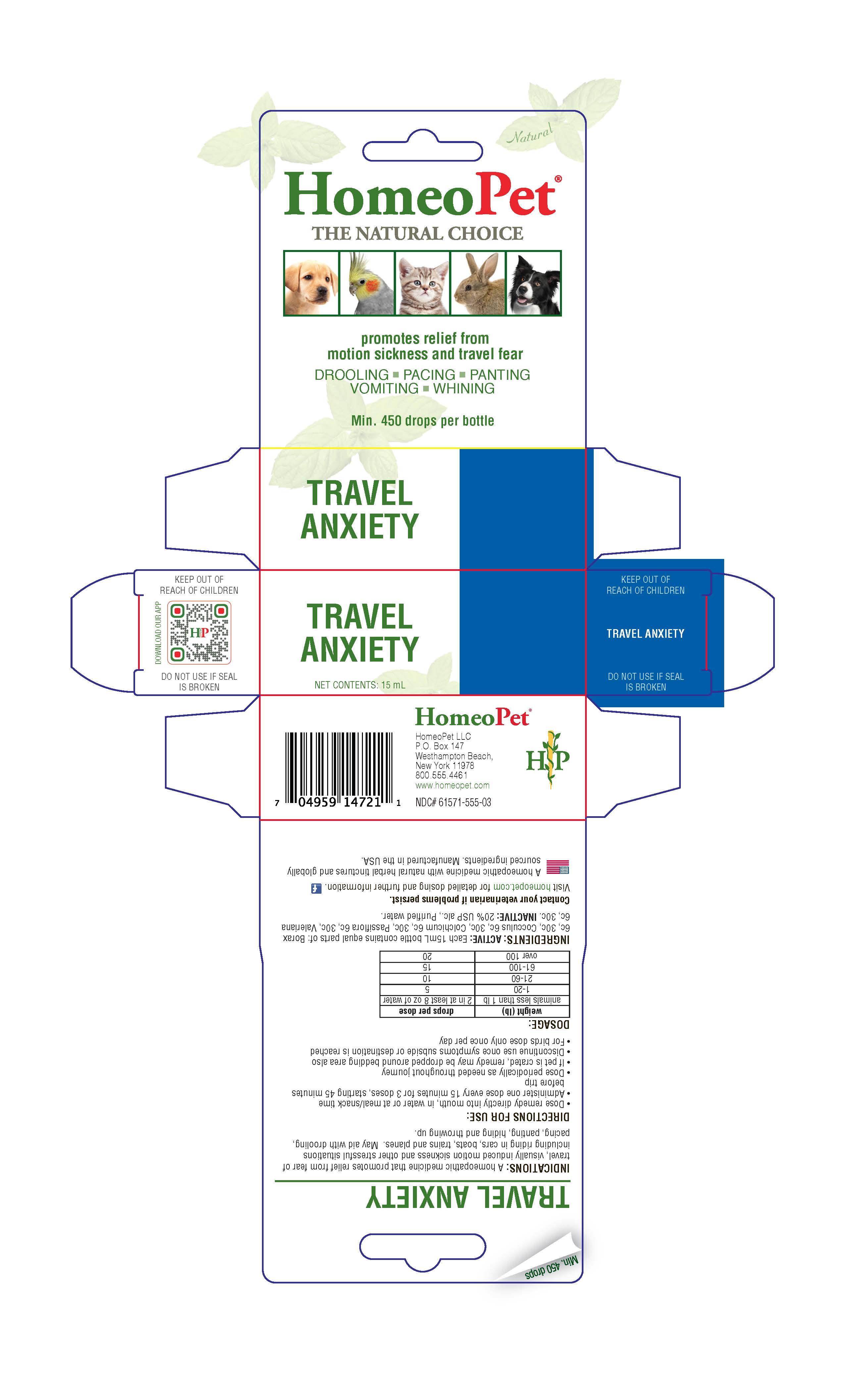 DRUG LABEL: Travel Anxiety
NDC: 61571-555 | Form: LIQUID
Manufacturer: HomeoPet, LLC
Category: homeopathic | Type: OTC ANIMAL DRUG LABEL
Date: 20221130

ACTIVE INGREDIENTS: SODIUM BORATE 6 [hp_C]/15 mL; ANAMIRTA COCCULUS SEED 6 [hp_C]/15 mL; COLCHICUM AUTUMNALE BULB 6 [hp_C]/15 mL; PASSIFLORA INCARNATA TOP 6 [hp_C]/15 mL; VALERIAN 6 [hp_C]/15 mL
INACTIVE INGREDIENTS: ALCOHOL; WATER

Travel Anxiety

Travel Anxiety

Promotes relief from motion sickness and travel fear

DROOLING-PACKING-PANTING

VOMITING-WHINING

Directions for Use and Dosage

- Dose remedy directly into mouth, in water or at meal/snack time
- Administer one dose every 15 minutes for 3 doses, starting 45 minutes before trip
- Dose periodically as needed throughout journey
- If pet is crated, remedy may be dropped around bedding area also
- Discontinue use once symptoms subside or destination is reached
- For birds dose only once per day

weight (lb) | drops per dose
animals less than 1 lb | 2 in at least 8 oz of water
1-20 | 5
21-60 | 10
61-100 | 15
over 100 | 20

Contact Veterinarian

Contact Veterinarian if problems persist.

Visit homeopet.com for detailed dosing and further information.

Ingredients HPUS: Active

Borax 6c, 30c, Cocculus 6c, 30c, Colchicum 6c, 30c, Passiflora 6c, 30c, Valeriana 6c, 30c

Inactive Ingredients

USP Alcohol, Purified Water

Indications

A natural homeopathic remedy that promotes relief from fear of travel, visually induced motion sickness and other stressful situations including riding in cars, boats, trains and planes. May aid with drooling, pacing, panting, hiding and throwing up.

PACKAGE LABEL

Add image transcription here...